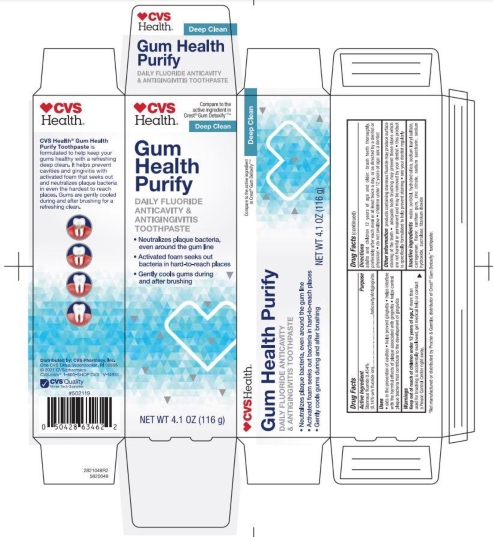 DRUG LABEL: Gum Detoxify
NDC: 69842-948 | Form: PASTE, DENTIFRICE
Manufacturer: CVS
Category: otc | Type: HUMAN OTC DRUG LABEL
Date: 20251113

ACTIVE INGREDIENTS: STANNOUS FLUORIDE 0.14 g/100 g
INACTIVE INGREDIENTS: ZINC CITRATE; TITANIUM DIOXIDE; SACCHARIN SODIUM; SODIUM HYDROXIDE; SORBITOL; HYDRATED SILICA; XANTHAN GUM; CARRAGEENAN; SODIUM LAURYL SULFATE; WATER; SUCRALOSE

5820048 CVS Gum Purify

ACTIVE INGREDIENT

Stannous fluoride 0.454% (0.14% w/v fluoride ion)

PURPOSE

Anticavity/Antigingivitis

INDICATIONS AND USAGE

* aids in the prevention of cavities * helps prevent gingivitis * helps interfere with the harmful effects of plaque associated with gingivitis * helps control plaque bacteria that contribute to the development of gingivitis

WARNINGS

Keep out of reach of children under 12 years of age. If more than used for brushing is accidentally swallowed, get medical help or contact a Poison Control Center right away.

DOSAGE AND ADMINISTRATION

adults and children 12 years of age adn older: brush teeth thoroughly, preferably each meal or at least twice a day, or as directed by a dentist or physician * do not swallow * children under 12 years of age: ask a dentist

OTHER SAFETY INFORMATION

products containing stannous fluoride may produce surface staining of the teeth * adequate tooth brushing may prevent these stains which are not harmful or permanent and may be removed by your dentist * this product is specifically formulated to help prevent staining * see your dentist regularly

INACTIVE INGREDIENT

water, sorbitol, hydrated silica, sodium lauryl sulfate, carrageenan, flavor, xanthan gum, zinc citrate, sodium saccharin, sodium hydroxide, sucralose, titanium dioxide